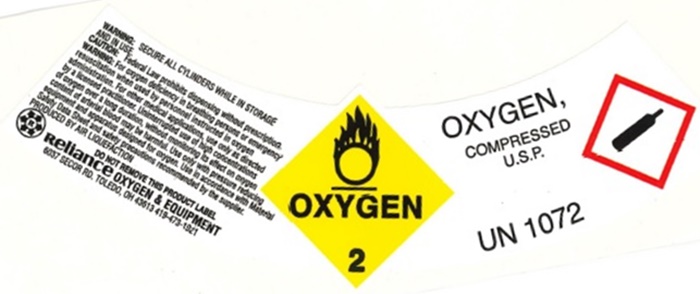 DRUG LABEL: Oxygen
NDC: 61362-2150 | Form: GAS
Manufacturer: Reliance Bottle Gas Company Inc. dba Reliance Oxygen & Equipment Co.
Category: prescription | Type: HUMAN PRESCRIPTION DRUG LABEL
Date: 20251024

ACTIVE INGREDIENTS: OXYGEN 99 L/100 L

OXYGEN COMPRESSED LABEL

WARNING: SECURE ALL CYLINDERS WILE IN STORAGE AND IN USE.

CAUTION: Federal Law prohibits dispensing without prescription.

WARNING: For oxygen deficiency in breathing persons or emergency resuscitation when used by personnel instructed in oxygen administration. For other medical applications. Use only as directed by licensed practitioner. Uninterrupted use of high concentrations of oxygen over a long duration, without monitoring its effect on oxygen content of arterial blood may be harmful. Use only with pressure reducing equipment and apparatus designed for oxygen. Use in accordance with Material Safety Data Sheet and safety precautions recommended by the supplier.

PRODUCE BY AIR LIQUIEFACTION

DO NOT REMOVE THIS PRODUCTY LABEL

Reliance OXYGEN & EQUIPENT

6037 SECOR RD. Toledo, OH 43613 419-473-1921

OXYGEN

2

OXYGEN,

COMPRESSED

U.S.P.

UN 1072